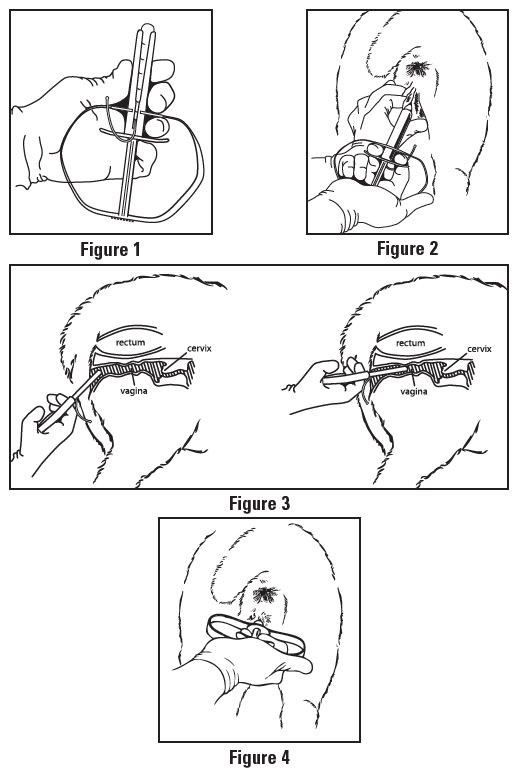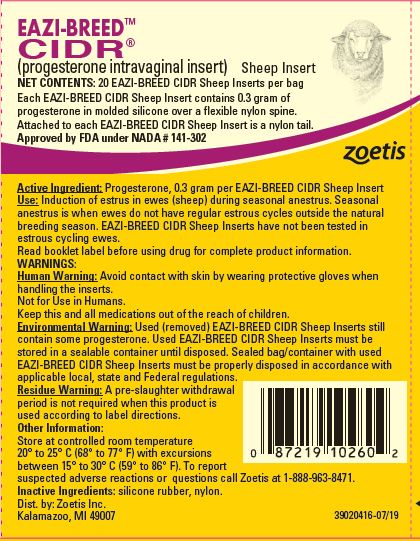 DRUG LABEL: EAZI-BREED CIDR Sheep
NDC: 54771-1533 | Form: INSERT, EXTENDED RELEASE
Manufacturer: Zoetis Inc.
Category: animal | Type: OTC ANIMAL DRUG LABEL
Date: 20220614

ACTIVE INGREDIENTS: PROGESTERONE 0.3 g/1 1

EAZI-BREED™ CIDR®
(progesterone)

Drug information

EAZI-BREED™

CIDR®

(progesterone intravaginal insert) Sheep Insert

NET CONTENTS: 20 EAZI-BREED CIDR Sheep Inserts per bag Each EAZI-BREED CIDR Sheep Insert contains 0.3 gram of progesterone in molded silicone over a flexible nylon spine. Attached to each EAZI-BREED CIDR Sheep Insert is a nylon tail.

Approved by FDA under NADA # 141-302

Active Ingredient

Progesterone, 0.3 gram per EAZI-BREED CIDR Sheep Insert

Use

Induction of estrus in ewes (sheep) during seasonal anestrus. Seasonal anestrus is when ewes do not have regular estrous cycles outside the natural breeding season. EAZI-BREED CIDR Sheep Inserts have not been tested in estrous cycling ewes.
Read booklet label before using drug for complete product information.

WARNINGS

Human Warning: Avoid contact with skin by wearing protective gloves when handling the inserts.
Not for Use in Humans.
Keep this and all medications out of the reach of children.
Environmental Warning: Used (removed) EAZI-BREED CIDR Sheep Inserts still contain some progesterone. Used EAZI-BREED CIDR Sheep Inserts must be stored in a sealable container until disposed. Sealed bag/container with used EAZI-BREED CIDR Sheep Inserts must be properly disposed in accordance with applicable local, state and Federal regulations.
Residue Warning: A pre-slaughter withdrawal period is not required when this product is used according to label directions.

Other Information

Store at controlled room temperature 20° to 25° C (68° to 77° F) with excursions between 15° to 30° C (59° to 86° F). To report suspected adverse reactions or questions call Zoetis at 1-888-963-8471.

Inactive Ingredients

silicone rubber, nylon.

Warnings

DO NOT USE
• in ewes with abnormal, immature or infected genital tracts
• in ewes that have never lambed
• an insert more than once. To prevent the potential transmission of venereal and blood borne diseases the EAZI-BREED CIDR Sheep Insert should be disposed after a single use.
WHEN USING THIS PRODUCT
• In ewes that respond to treatment the onset of estrus generally occurs within 1 to 3 days after removal of the EAZI-BREED CIDR Sheep Insert.
• Make sure to have a sufficient number of rams to adequately breed all ewes with an induced estrus. Breeds of rams may vary in libido in the non-breeding season. Therefore a ewe to ram ratio up to 18:1 is recommended for multi-sire situations. For single sire lots, 12:1 for ram lambs and up to 18:1 for yearling rams are recommended.
YOU MAY NOTICE:
Clear, cloudy, yellow or bloody mucus on the outside of EAZI-BREED CIDR Sheep Insert when removed from ewes. The mucus may have an offensive odor. This is a result of mild irritation to the vaginal lining by the presence of the EAZI-BREED CIDR Sheep Insert, and generally clears between the time of removal and breeding. Such irritation does not affect fertility.

DIRECTIONS

For induction of estrus in ewes (sheep) during seasonal anestrus:

• Administer one EAZI-BREED CIDR Sheep Insert per ewe for 5 days.

• After insert removal, use standard flock breeding procedures to breed ewes at induced estrus.

Insertion

1. Avoid contact with skin by wearing protective gloves when handling inserts.
2. Only use the specially designed EAZI-BREED CIDR Sheep Insert Applicator for administration.
3. Restrain ewes appropriately prior to administration.
4. Wash the applicator in a non-irritating antiseptic solution, and then apply a veterinary obstetrical lubricant to the end of the applicator.
5. Push the tail end of the EAZI-BREED CIDR Sheep Insert into the applicator taking care to assure the tail is extending upward through the slot of the applicator and is pointed away from the handle.
6. Fold the wings of the EAZI-BREED CIDR Sheep Insert to make it longer and continue to advance the insert into the applicator until it is fully seated with only the tips of the wings protruding from the end of the applicator (see Figure 1).
7. Lubricate the protruding tips of the wings of the EAZI-BREED CIDR Sheep Insert with veterinary obstetrical lubricant.
8. Clean the exterior of the vulva with disposable tissue.
9. Open the lips of the vulva and gently place the loaded applicator through the vulva. The slot in the applicator should face down (see Figure 2).
10. Once the loaded applicator is past the vulva slope the applicator slightly upwards (35 - 45° angle) by lowering the handle, and then forward, without forcing, until the applicator is fully inserted or resistance is felt (see Figure 3).
11. Squeeze the finger grips within the handle of the applicator to deposit the EAZI-BREED CIDR Sheep Insert in the anterior vagina (see Figure 4) and then pull the applicator backwards to remove it from the vagina.
12. With the EAZI-BREED CIDR Sheep Insert correctly placed, with the wings open in the anterior portion of the vagina, the tail of the insert should be visible, pointing downward from the vulva of the ewe.

Removal

1. Remove EAZI-BREED CIDR Sheep Inserts by pulling, gently but firmly, on the protruding nylon tail.
2. EAZI-BREED CIDR Sheep Inserts may reverse direction within the vagina; therefore, if the nylon tail of the insert is not visible on the day of removal, check the vagina to determine if an insert is present.
3. Used (removed) EAZI-BREED CIDR Sheep Inserts must be stored in a sealable container until disposed. Sealed bag/container with used EAZI-BREED CIDR Sheep Inserts must be properly disposed in accordance with applicable local, state and Federal regulations.

Restricted Drug (California) - use only as directed
zoetis
Distributed by:
Zoetis Inc.
Kalamazoo, MI 49007
EAZI-BREED is a trademark and CIDR is a registered trademark of DEC International NZ Ltd.
39020416-07/19